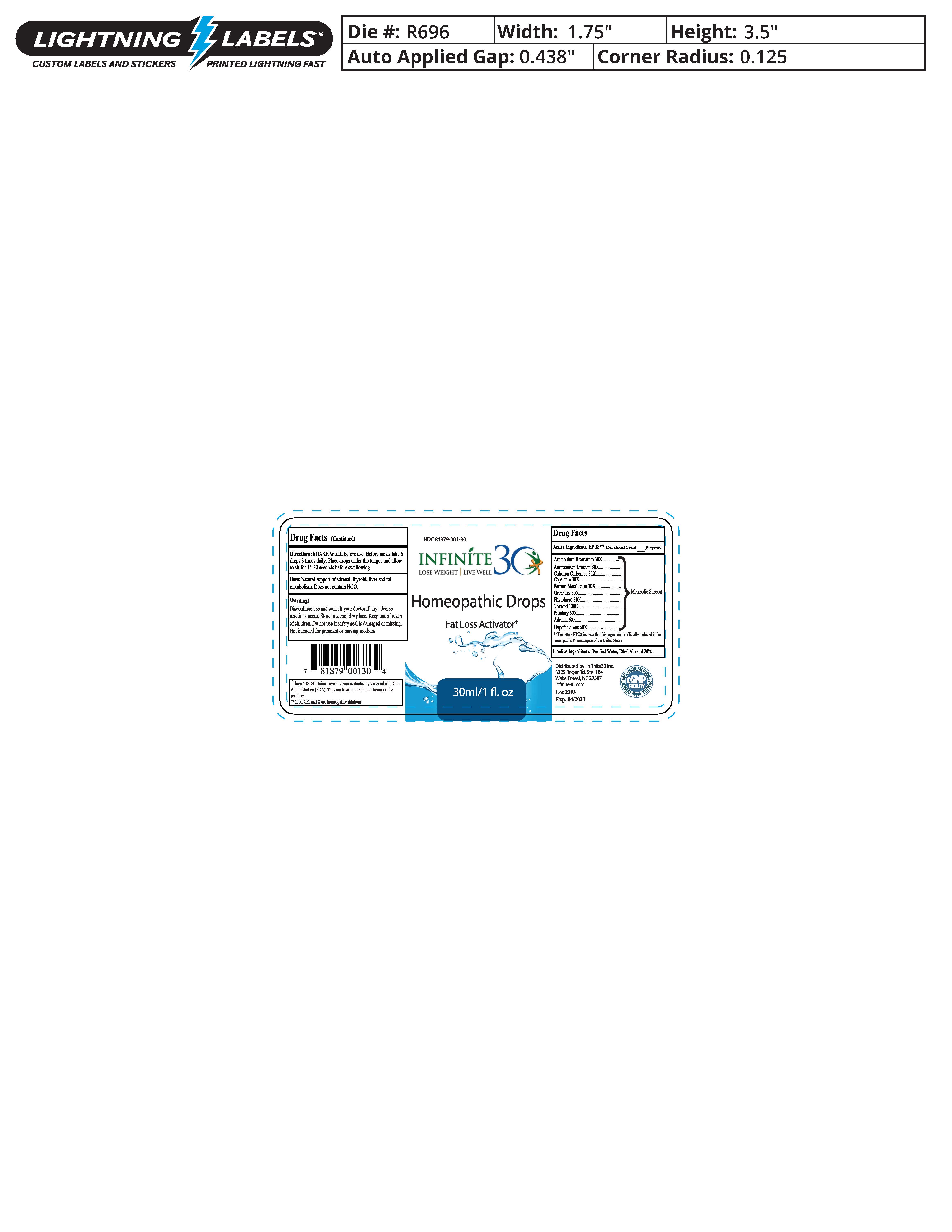 DRUG LABEL: Fat Loss Activator
NDC: 81879-001 | Form: SOLUTION/ DROPS
Manufacturer: Infinite30 LLC
Category: homeopathic | Type: HUMAN OTC DRUG LABEL
Date: 20210510

ACTIVE INGREDIENTS: IRON 30 [hp_X]/1 1; AMMONIUM BROMIDE 30 [hp_X]/1 1; CAPSICUM 30 [hp_X]/1 1; GRAPHITE 30 [hp_X]/1 1; PHYTOLACCA AMERICANA ROOT 30 [hp_X]/1 1; OYSTER SHELL CALCIUM CARBONATE, CRUDE 30 [hp_X]/1 1; EPINEPHRINE 60 [hp_X]/1 1; BOS TAURUS HYPOTHALAMUS 60 [hp_X]/1 1; BOS TAURUS PITUITARY GLAND 60 [hp_X]/1 1; THYROID, UNSPECIFIED 100 [hp_C]/1 1; ANTIMONY SULFATE 30 [hp_X]/1 1
INACTIVE INGREDIENTS: WATER; ALCOHOL

Drug facts

Active Ingredients | Purposes
Ammonium Bromatum 30X | Metabolic Support
Antimonium Crudum 30X | Metabolic Support
Calcarea Crudum 30X | Metabolic Support
Capsicum 30X | Metabolic Support
Ferrum Metallicum 30X | Metabolic Support
Graphites 30X | Metabolic Support
Phytolacca 30X | Metabolic Support
Thyroid 100C | Metabolic Support
Pituitary 60X | Metabolic Support
Adrenal 60X | Metabolic Support
Hypothalamus 60X | Metabolic Support

Inactive Ingredients

Purified water, ethyl alcohol 20%

Directions

SHAKE WELL before use. Before meals take 5 drops 3 times daily. Place drops under the tongue and allow to sit for 15-20 seconds before swallowing.

INDICATIONS AND USAGE

Natural support of adrenal, thyroid, liver, and fat metabolism

Uses

Natural support of adrenal, thyroid, liver and fat metabolism. Does not contain HCG

Warnings

Discontinue use and consult your doctor if any adverse reactions occur. Store in a cool dry place. Keep out of reach of children. Do not use if safety seal is damaged or missing. Not intended for pregnant or nursing mothers.

Keep out of reach of children.